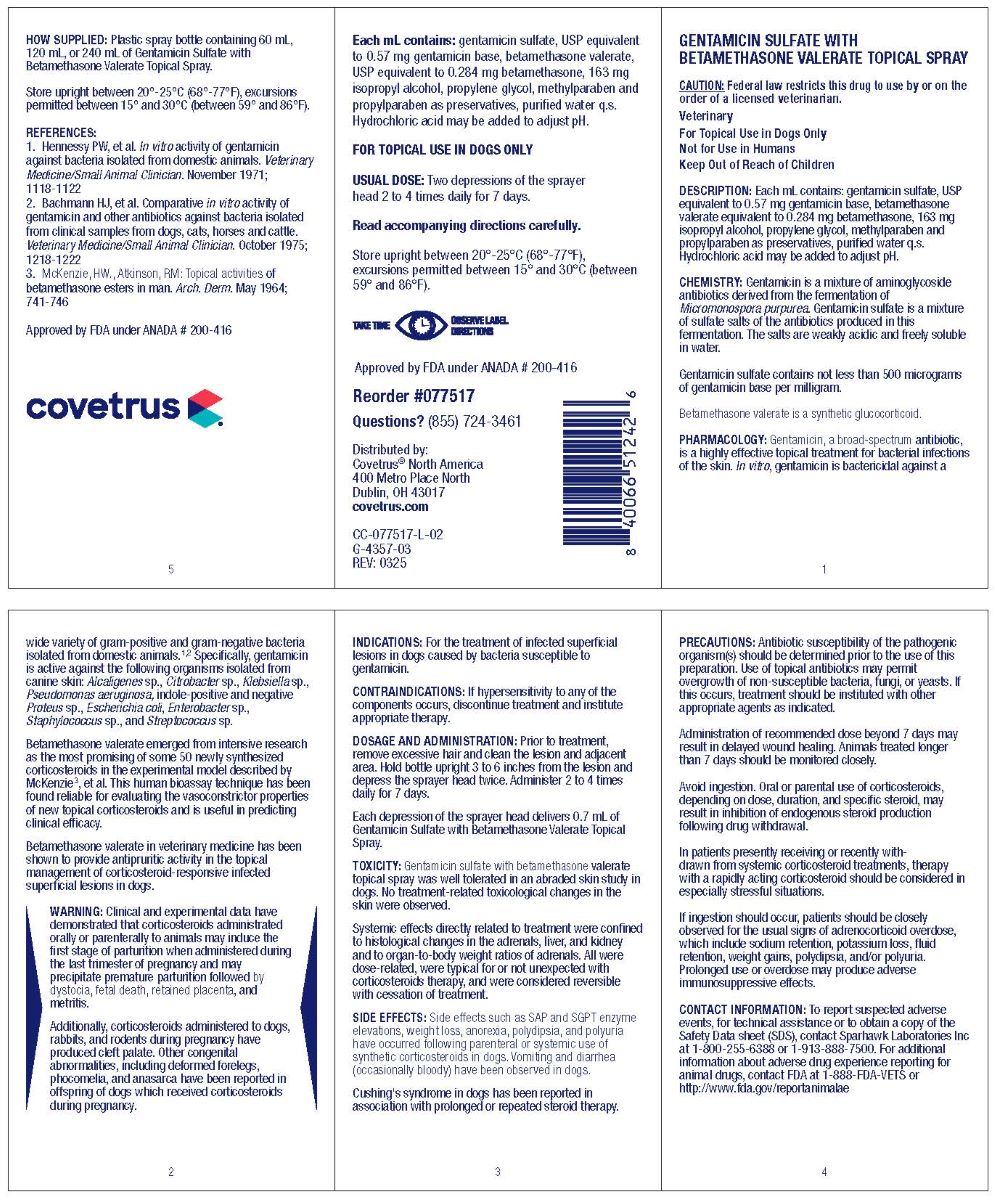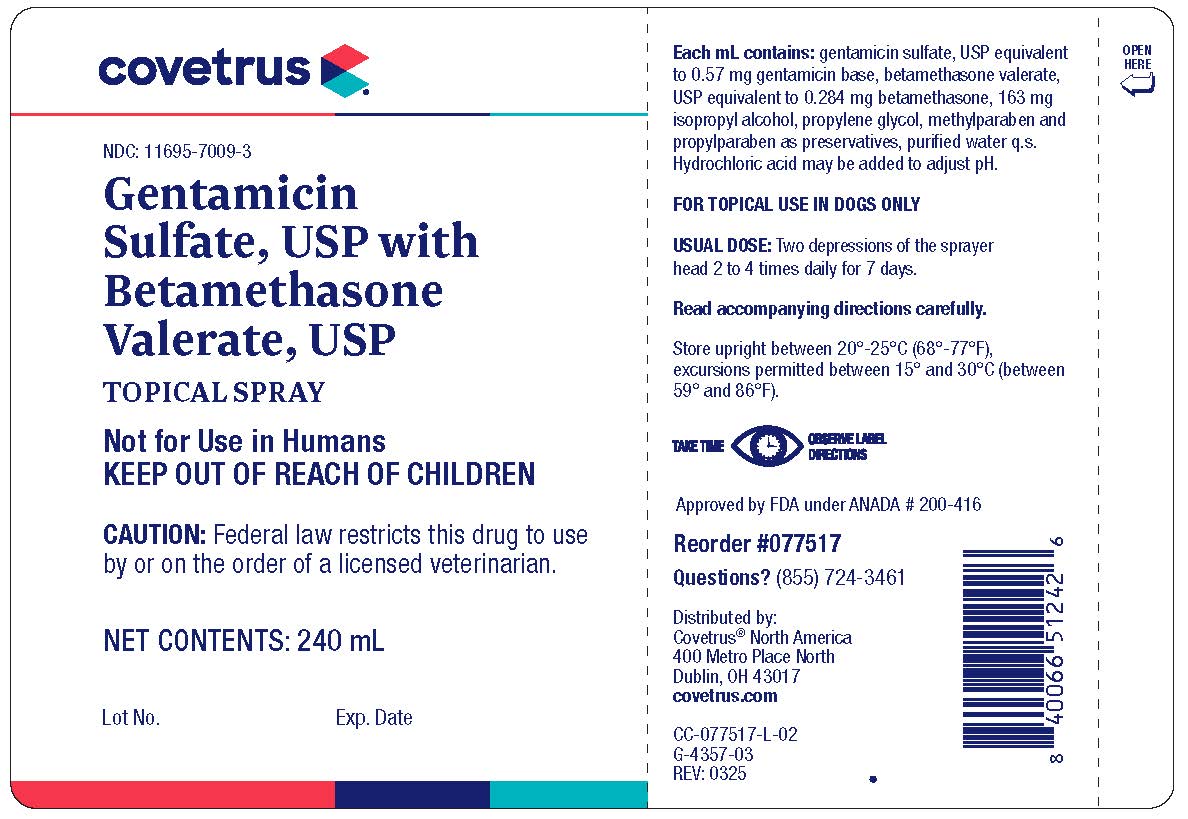 DRUG LABEL: Gentamicin Sulfate
NDC: 11695-7009 | Form: SPRAY
Manufacturer: Covetrus North America
Category: animal | Type: PRESCRIPTION ANIMAL DRUG LABEL
Date: 20250623

ACTIVE INGREDIENTS: GENTAMICIN SULFATE 0.57 mg/1 mL; BETAMETHASONE VALERATE 0.284 mg/1 mL

Gentamicin Sulfate With Betamethasone Valerate TOPICAL SPRAY

DESCRIPTION

GENTAMICIN SULFATE WITH
BETAMETHASONE VALERATE TOPICAL SPRAY
CAUTION: Federal law restricts this drug to use by or on the
order of a licensed veterinarian.
Veterinary
For Topical Use in Dogs Only
Not for Use in Humans
Keep Out of Reach of Children

Each mL contains: gentamicin sulfate, USP equivalent
to 0.57 mg gentamicin base, betamethasone valerate,
USP equivalent to 0.284 mg betamethasone, 163 mg
isopropyl alcohol, propylene glycol, methylparaben and
propylparaben as preservatives, purified water q.s.
Hydrochloric acid may be added to adjust pH.

CLINICAL PHARMACOLOGY

CHEMISTRY

Gentamicin is a mixture of aminoglycoside antibiotics derived from the fermentation of Micromonospora purpurea. Gentamicin sulfate is a mixture of sulfate salts of the antibiotics produced in this fermentation. The salts are weakly acidic and freely soluble in water.

Gentamicin sulfate contains not less than 500 micrograms of gentamicin base per milligram.

Betamethasone valerate is a synthetic glucocorticoid.

PHARMACOLOGY

Gentamicin, a broad-spectrum antibiotic, is a highly effective topical treatment for bacterial infections of the skin. In vitro, gentamicin is bactericidal against a wide variety of gram-positive and gram-negative bacteria isolated from domestic animals.^1,2 Specifically, gentamicin is active against the following organisms isolated from canine skin: Alcaligenes sp., Citrobacter sp., Klebsiella sp., Pseudomonas aeruginosa, indole-positive and negative Proteus sp., Escherichia coli, Enterobacter sp., Staphylococcus sp., and Streptococcus sp.

Betamethasone valerate emerged from intensive research as the most promising of some 50 newly synthesized corticosteroids in the experimental model described by McKenzie^3, et al. This human bioassay technique has been found reliable for evaluating the vasoconstrictor properties of new topical corticosteroids and is useful in predicting clinical efficacy.

Betamethasone valerate in veterinary medicine has been shown to provide anti-inflammatory and antipruritic activity in the topical management of corticosteroid-responsive infected superficial lesions in dogs.

WARNINGS

Clinical and experimental data have demonstrated that corticosteriods administrated orally or parenterally to animals may induce the first stage of parturition when administered during the last trimester of pregnancy and may precipitate premature parturition followed by dystocia, fetal death, retained placenta, and metritis.

Additionally, corticosteroids administered to dogs, rabbits and rodents during pregnancy have produced cleft palate. Other congenital abnormalities including deformed forelegs, phocomelia, and anasarca have been reported in offspring of dogs which received corticosteroids during pregnancy.

INDICATIONS

For the treatment of infected superficial lesions in dogs caused by bacteria susceptible to gentamicin.

CONTRAINDICATIONS

If hypersensitivity to any of the components occurs, discontinue treatment and institute appropriate therapy.

DOSAGE AND ADMINISTRATION

FOR TOPICAL USE IN DOGS ONLY

Prior to treatment, remove excessive hair and clean the lesion and adjacent area. Hold bottle upright 3 to 6 inches from the lesion and depress the sprayer head twice. Administer 2 to 4 times daily for 7 days.
Each depression of the sprayer head delivers 0.7 mL of Gentamicin sulfate, USP with betamethasone valerate, USP.

TOXICITY

Gentamicin Sulfate with betamethasone valerate topical spray was well tolerated in a abraded skin study in dogs. No treatment-related toxicological changes in the skin were observed.

Systemic effects directly related to treatment were confined to histological changes in the adrenals, liver and kidney and to organ-to-body weight ratios of adrenals. All were dose related, were typical for or not unexpected with corticosteroids therapy, and were considered reversible with cessation of treatment.

SIDE EFFECTS

Side effects such as SAP and SGPT enzyme elevations, weight loss, anorexia, polydipsia, and polyuria have occurred following parenteral or systemic use of synthetic corticosteroids in dogs. Vomiting and diarrhea (occasionally bloody) have been observed in dogs.

Cushings syndrome in dogs has been reported in association with prolonged or repeated steroid therapy.

PRECAUTIONS

Antibiotic susceptibility of the pathogenic organism(s) should be determined prior to the use of this preparation. Use of topical antibiotics may permit overgrowth of non-susceptible bacteria, fungi, or yeasts. If this occurs, treatment should be instituted with other appropriate agents as indicated.

Administration of recommended dose beyond 7 days may result in delayed wound healing. Animals treated longer than 7 days should be monitored closely.

Avoid ingestion. Oral or parental use of corticosteroids depending on dose, duration, and specific steroid may result in inhibition of endogenous steroid production following drug withdrawal.

In patients presently receiving or recently withdrawn from system corticosteroid treatments, therapy with a rapidly acting corticosteroid should be considered in especially stressful situations.

If ingestion should occur, patients should be closely observed for the usual signs of adrenocorticoid overdose which includes sodium retention, potassium loss, fluid retention, weight gains, polydipsia, and/or polyuria. Prolonged use or overdose may produce adverse immunosuppressive effects.

CONTACT INFORATION

To report suspected adverse events, for technical assistance or to obtain a copy of the Safety Data sheet (SDS), contact Sparhawk Laboratories Inc at 1-800-255-6388 or 1-913-888-7500. For additional information about adverse drug experience reporting for animal drugs, contact FDA at 1-888-FDA-VETS or http://www.fda.gov/reportanimalae

HOW SUPPLIED

Plastic spray bottle containing 60 mL, 120 mL, or 240 mL of Gentamicin Topical Spray.

STORAGE AND HANDLING

Store upright between 20o-25oC (68o-77oF), excursions permitted between 15o and 30o (between 59o and 86oF).

TAKE TIME OBSERVE LABEL DIRECTIONS.

REFERENCES

1. Hennessy PW, et al. In vitro activity of gentamicin against bacteria isolated from domestic animals. Veterinary Medicine/Small Animal Clinician. November 1971; 1118-1122

2. Bachmann HJ, et al. Comparative in vitro activity of gentamicin and other antibiotics against bacteria isolated from clinical samples from dogs, cats, horses and cattle. Veterinary Medicine/Small Animal Clinician. October 1975; 1218-1222

3. McKenzie, HW., Atkinson, RM: Topical activities of betamethasone esters in man. Arch. Derm. May 1964; 741-746